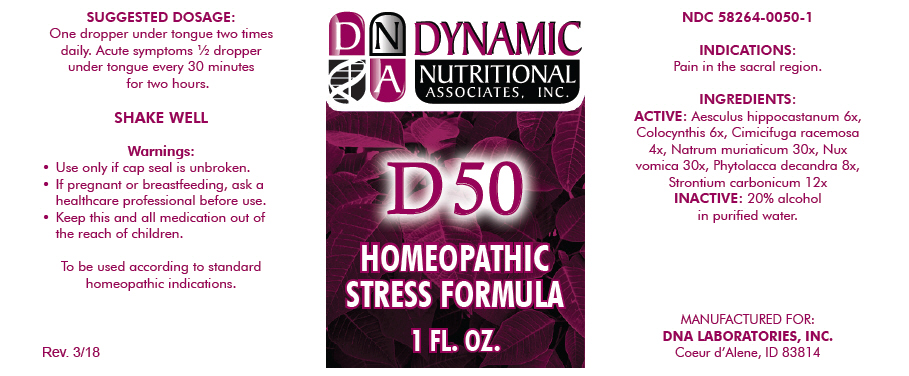 DRUG LABEL: D-50
NDC: 58264-0050 | Form: SOLUTION
Manufacturer: DNA Labs, Inc.
Category: homeopathic | Type: HUMAN OTC DRUG LABEL
Date: 20250113

ACTIVE INGREDIENTS: HORSE CHESTNUT 6 [hp_X]/1 mL; CITRULLUS COLOCYNTHIS FRUIT PULP 6 [hp_X]/1 mL; BLACK COHOSH 4 [hp_X]/1 mL; SODIUM CHLORIDE 30 [hp_X]/1 mL; STRYCHNOS NUX-VOMICA SEED 30 [hp_X]/1 mL; PHYTOLACCA AMERICANA ROOT 8 [hp_X]/1 mL; STRONTIUM CARBONATE 12 [hp_X]/1 mL
INACTIVE INGREDIENTS: ALCOHOL; WATER

D-50

NDC 58264-0050-1

INDICATIONS

PURPOSE

Pain in the sacral region.

INGREDIENTS

ACTIVE

Aesculus hippocastanum 6x, Colocynthis 6x, Cimicifuga racemosa 4x, Natrum muriaticum 30x, Nux vomica 30x, Phytolacca decandra 8x, Strontium carbonicum 12x

INACTIVE

20% alcohol in purified water.

SUGGESTED DOSAGE

One dropper under tongue two times daily. Acute symptoms ½ dropper under tongue every 30 minutes for two hours.

STORAGE AND HANDLING

SHAKE WELL

Warnings

- Use only if cap seal is unbroken.

PREGNANCY OR BREAST FEEDING

- If pregnant or breastfeeding, ask a healthcare professional before use.

KEEP OUT OF REACH OF CHILDREN

- Keep this and all medication out of the reach of children.

To be used according to standard homeopathic indications.

PRINCIPAL DISPLAY PANEL - 1 FL. OZ. Bottle Label

DYNAMIC
NUTRITIONAL
ASSOCIATES, INC.

D 50

HOMEOPATHIC
STRESS FORMULA

1 FL. OZ.